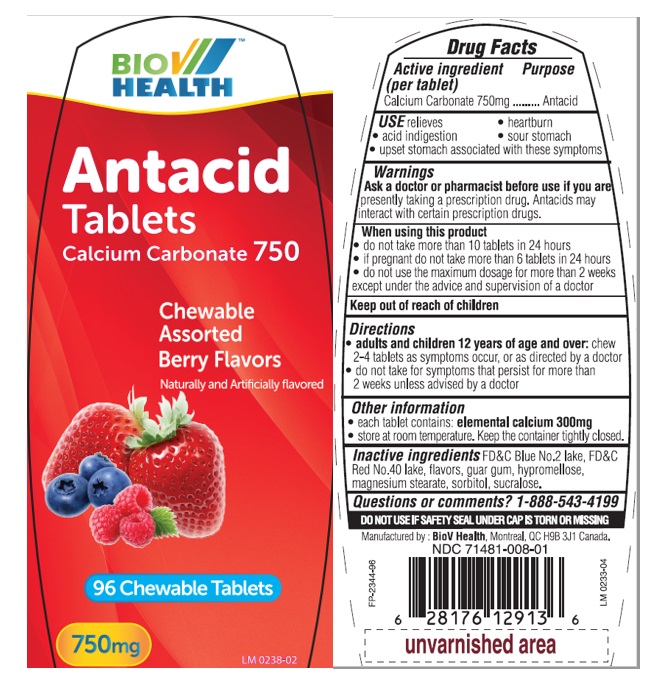 DRUG LABEL: Bio V Antacid Berry 96ct
NDC: 71481-008 | Form: TABLET
Manufacturer: BioV Health Inc
Category: otc | Type: HUMAN OTC DRUG LABEL
Date: 20240404

ACTIVE INGREDIENTS: CALCIUM CARBONATE 750 mg/1 1
INACTIVE INGREDIENTS: FD&C BLUE NO. 2--ALUMINUM LAKE; FD&C RED NO. 40; GUAR GUM; HYPROMELLOSE, UNSPECIFIED; MAGNESIUM STEARATE; SORBITOL; SUCRALOSE

Bio V Antacid Berry Flavors

Active ingredient (per tablet)

Calcium Carbonate 750mg

Purpose

Antacid

USE

Relieves • acid indigestion • heartburn • sour stomach • upset stomach associated with these symptoms

Warnings

Ask a doctor or pharmacist before use if you arepresently taking a prescription drug. Antacids may interact with certain prescription drugs.

When using this product

- do not take more than 10 tablets in 24 hours.
- if pregnant do not take more than 6 tablets in 24 hours.
- do not use the maximum dosage for more than 2 weeks except under the advice and supervision of a doctor.

Keep out of of reach of children

Directions

- adults and children 12 years of age and over:chew 2-4 tablets as symtoms occur, or as directed by a doctor
- do not take for symtoms that persist for more than 2 weeks unless advised by a doctor

Other information

- each tablet contains: elemental calcium 300 mg.
- Store at room temperature. Keep the container tightly closed.

Inactive ingredients

FD&C Blue No.2 lake, FD&C Red No.40 lake, flavors, guar gum, hypromellose, magnesium stearate, sorbitol, sucralose.

Questions or comments?

1-888-543-4199